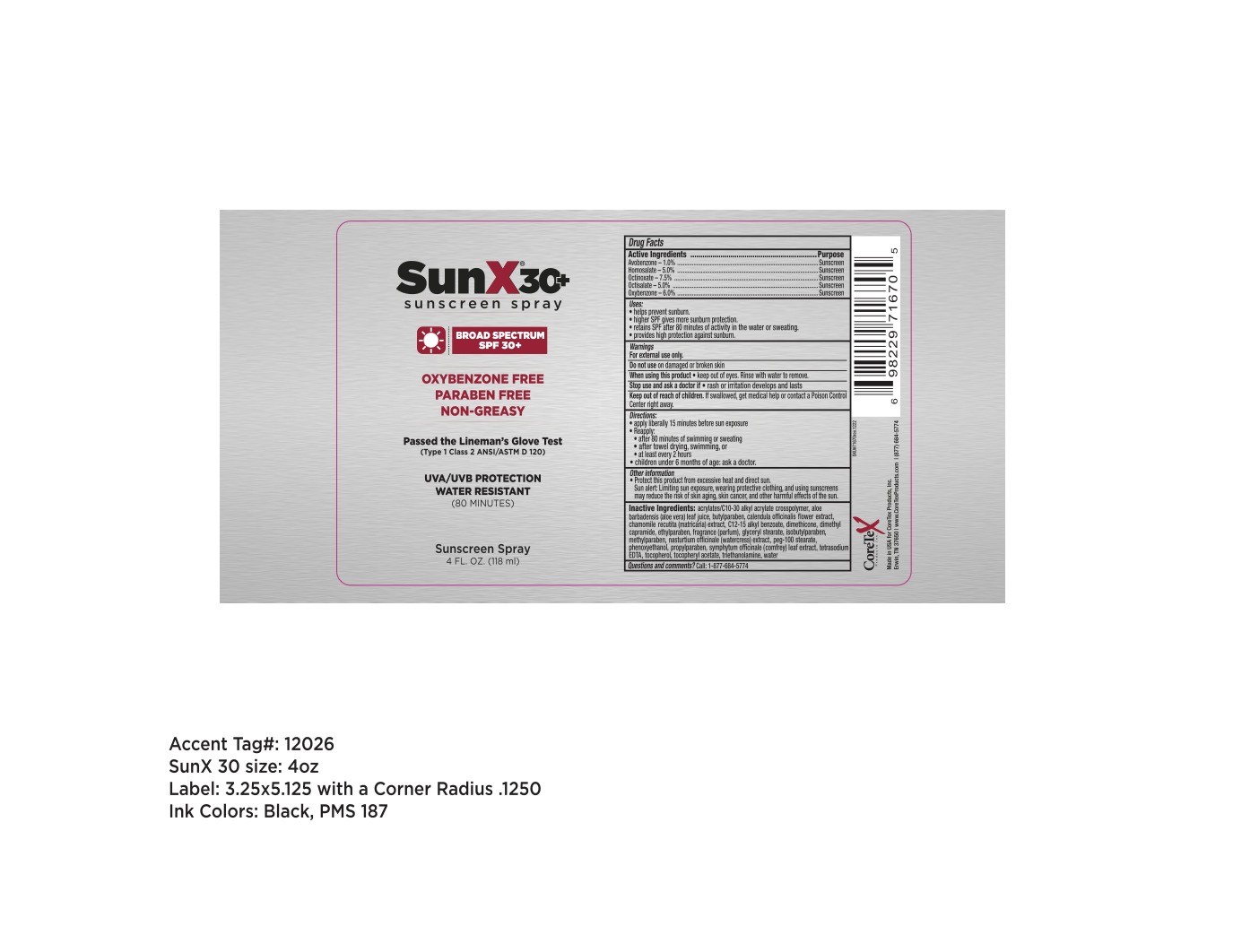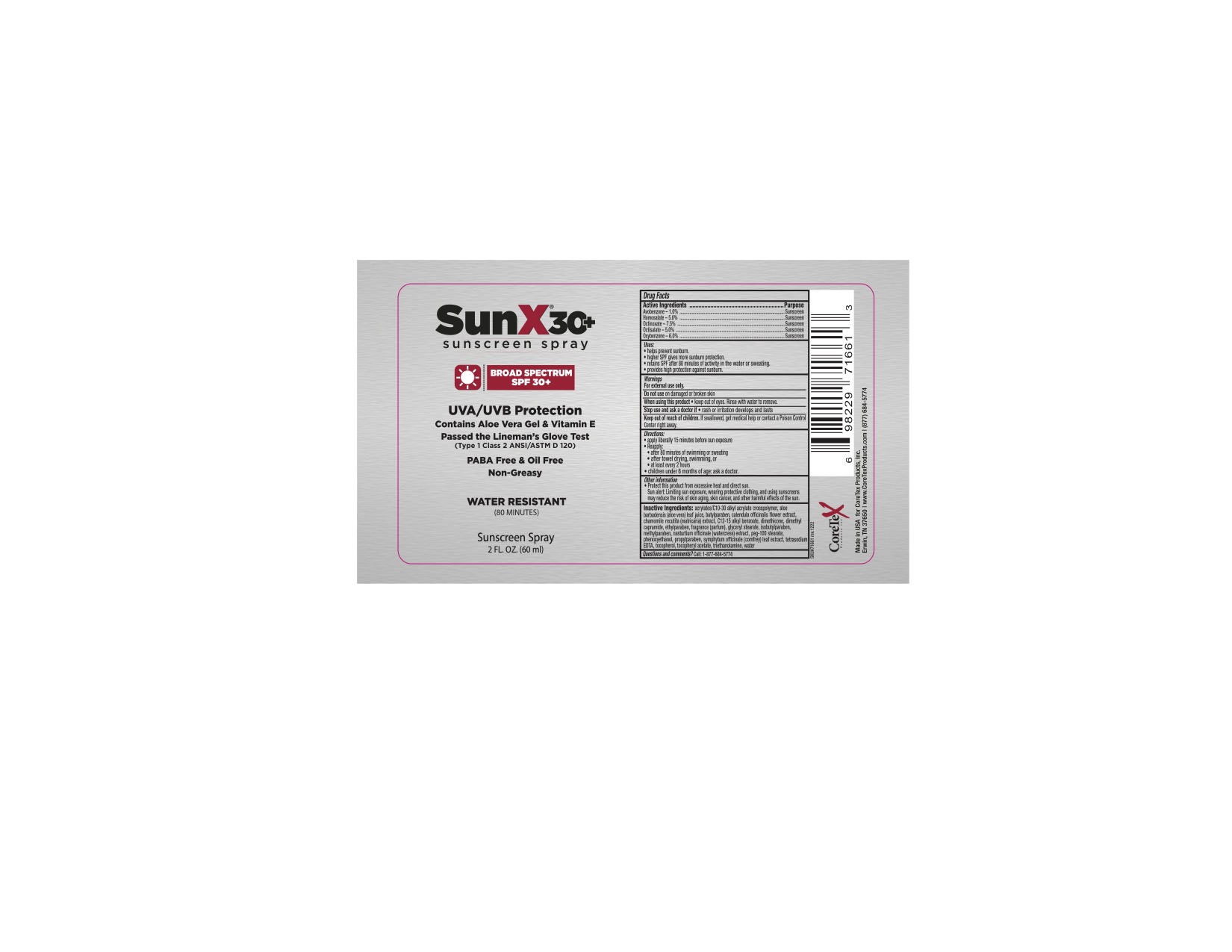 DRUG LABEL: CoreTex Sun X SPF 30 Thin
NDC: 65753-101 | Form: LIQUID
Manufacturer: CoreTex Products Inc
Category: otc | Type: HUMAN OTC DRUG LABEL
Date: 20231022

ACTIVE INGREDIENTS: AVOBENZONE 1 g/100 mL; HOMOSALATE 5 g/100 mL; OCTINOXATE 7.5 g/100 mL; OCTISALATE 5 g/100 mL; OXYBENZONE 6 g/100 mL
INACTIVE INGREDIENTS: WATER; DIMETHYL CAPRAMIDE; DIMETHICONE; ALOE VERA LEAF; .ALPHA.-TOCOPHEROL; TROLAMINE; PROPYLPARABEN; PHENOXYETHANOL; GLYCERYL MONOSTEARATE; METHYLPARABEN; ETHYLPARABEN; BUTYLPARABEN; ISOBUTYLPARABEN; ALKYL (C12-15) BENZOATE; CHAMOMILE; CALENDULA OFFICINALIS FLOWER; PEG-100 STEARATE; NASTURTIUM OFFICINALE; COMFREY LEAF; .ALPHA.-TOCOPHEROL ACETATE; TETRASODIUM EDETATE DIHYDRATE; FRAGRANCE 13576; ACRYLATES CROSSPOLYMER-6

Sun X SPF 30 Thin
65753-101

Active ingredients

Avobenzone 1.0%

Homosalate 5.0%

Octinoxate 7.5%

Octisalate 5.0%

Oxybenzone 6.0%

Purpose

Sunscreen

Sunscreen

Sunscreen

Sunscreen

Sunscreen

Uses

- helps prevent sunburn
- higher SPF gives more sunburn protection.
- retains SPF after 80 minutes of activity in the water or sweating
- provides high protection against sunburn.

Warnings

For external use only.

Do not use

- on damaged or broken skin

When using this product

- keep out of the eye. Rinse with water to remove.

Stop use and ask a doctor if

- rash or irritation develops and lasts

Keep out of the reach of children.

If swallowed, get medical help or contact a Poison Control Center right away.

Directions:

- apply liberally 15 minutes before sun exposure

- Reapply:
- after 80 minutes of swimming or sweating
  - after towel drying, swimming, or
  - at least every 2 hours

- children under 6 months of age: ask a doctor.

Other information

- protect this product from excessive heat and direct sun.

Sun alert: Limiting sun exposure, wearing protective clothing, and using sunscreens may reduce the risk of skin aging, skin cancer, and other harmful effects of the sun.

Inactive ingredients:

acrylates/C10-30 alkyl acrylate crosspolymer, aloe barbadensis (aloe vera) leaf juice, butylparaben, calendula officinalis flower extract, carbomer, chamomile recutita (matricaria) extract, C12-15 alkyl benzoate, dimethicone, dimethyl capramide, ethylparaben, fragrance (parfum), glyceryl stearate, isobutylparaben, methylparaben, nasturtium officinale (watercress) extract, peg-100 stearate, phenoxyethanol, propylparaben, symphytum officinale (comfrey) leaf extract, tetrasodium EDTA, tocopherol, tocopheryl acetate, triethanolamine, water

Questions and comments?

Call: 1-877-684-5774